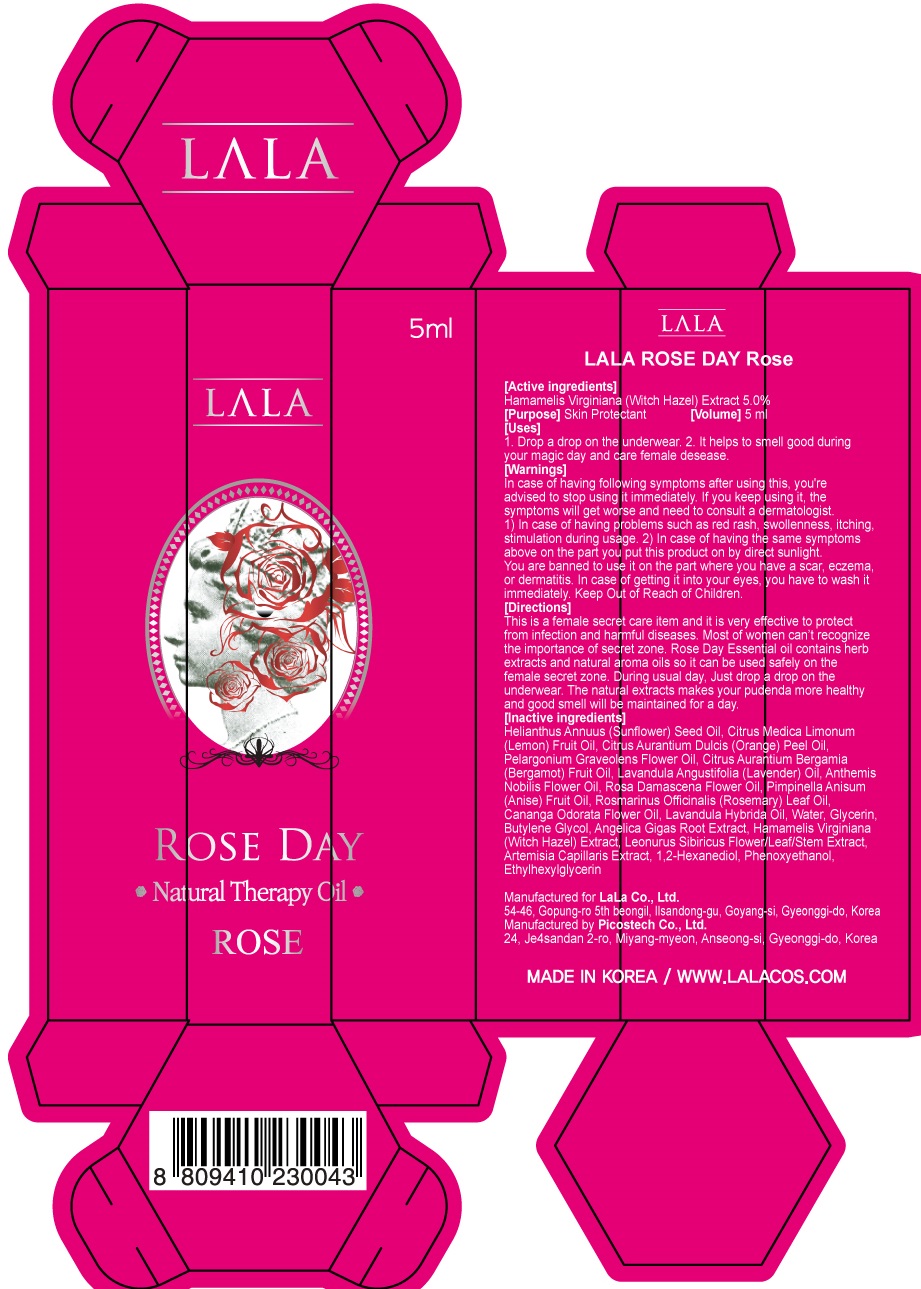 DRUG LABEL: Roseday Rose
NDC: 55885-020 | Form: LIQUID
Manufacturer: LaLa Co., Ltd.
Category: otc | Type: HUMAN OTC DRUG LABEL
Date: 20170925

ACTIVE INGREDIENTS: Witch Hazel 0.25 g/5 mL
INACTIVE INGREDIENTS: Water; Glycerin

ACTIVE INGREDIENT

Active ingredients: Hamamelis Virginiana (Witch Hazel) Extract 5.0%

PURPOSE

Purpose: Skin Protectant

INACTIVE INGREDIENT

Inactive ingredients: Helianthus Annuus (Sunflower) Seed Oil, Citrus Medica Limonum (Lemon) Fruit Oil, Citrus Aurantium Dulcis (Orange) Peel Oil, Pelargonium Graveolens Flower Oil, Citrus Aurantium Bergamia (Bergamot) Fruit Oil, Lavandula Angustifolia (Lavender) Oil, Anthemis Nobilis Flower Oil, Rosa Damascena Flower Oil, Pimpinella Anisum (Anise) Fruit Oil, Rosmarinus Officinalis (Rosemary) Leaf Oil, Cananga Odorata Flower Oil, Lavandula Hybrida Oil, Water, Glycerin, Butylene Glycol, Angelica Gigas Root Extract, Leonurus Sibiricus Flower/Leaf/Stem Extract, Artemisia Capillaris Extract, 1,2-Hexanediol, Phenoxyethanol, Ethylhexylglycerin

WARNINGS

Warnings: In case of having following symptoms after using this, you're advised to stop using it immediately. If you keep using it, the symptoms will get worse and need to consult a dermatologist. 1) In case of having problems such as red rash, swollenness, itching, stimulation during usage. 2) In case of having the same symptoms above on the part you put this product on by direct sunlight. You are banned to use it on the part where you have a scar, eczema, or dermatitis. In case of getting it into your eyes, you have to wash it immediately.

KEEP OUT OF REACH OF CHILDREN

Uses

Uses: 1. Drop a drop on the underwear. 2. It helps to smell good during your magic day and care female desease.

Directions

Directions: This is a female secret care item and it is very effective to protect from infection and harmful diseases. Most of women can’t recognize the importance of secret zone. Rose Day Essential oil contains herb extracts and natural aroma oils so it can be used safely on the female secret zone. During usual day, Just drop a drop on the underwear. The natural extracts makes your pudenda more healthy and good smell will be maintained for a day.